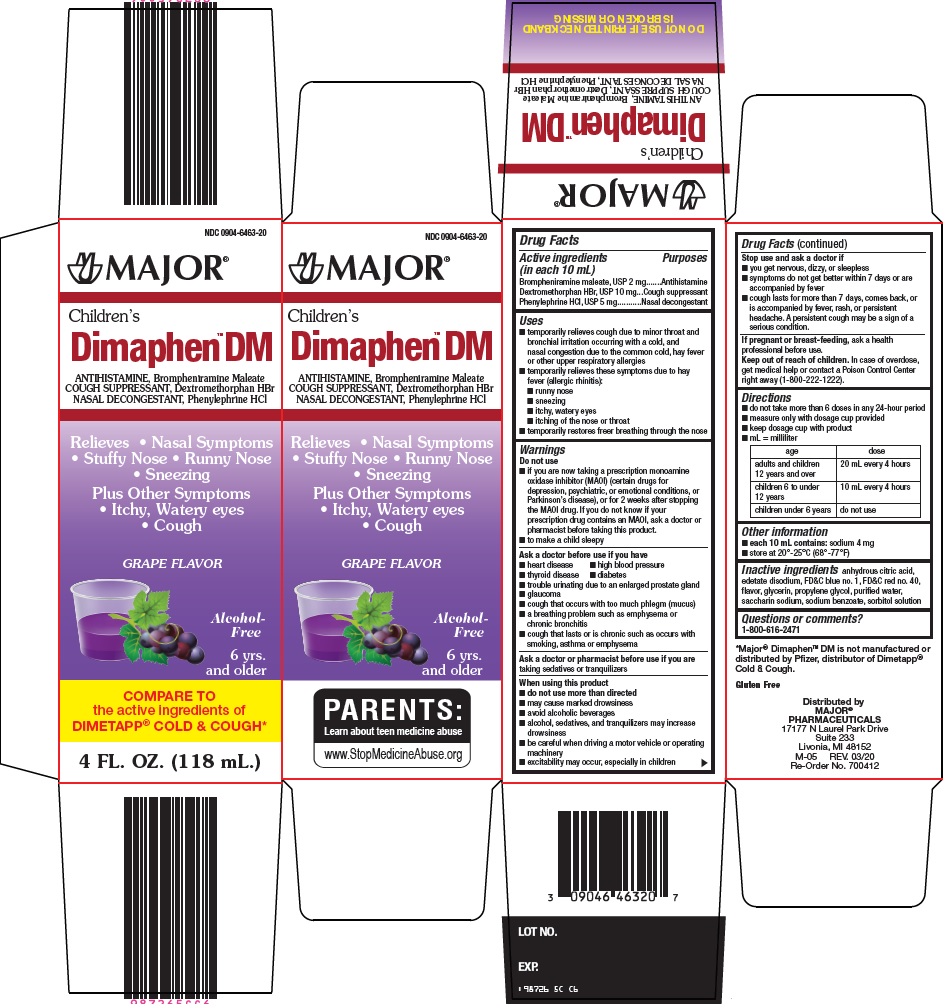 DRUG LABEL: dimaphen dm
NDC: 0904-6463 | Form: SOLUTION
Manufacturer: Major Pharmaceuticals
Category: otc | Type: HUMAN OTC DRUG LABEL
Date: 20260225

ACTIVE INGREDIENTS: BROMPHENIRAMINE MALEATE 2 mg/10 mL; DEXTROMETHORPHAN HYDROBROMIDE 10 mg/10 mL; PHENYLEPHRINE HYDROCHLORIDE 5 mg/10 mL
INACTIVE INGREDIENTS: ANHYDROUS CITRIC ACID; EDETATE DISODIUM; FD&C BLUE NO. 1; FD&C RED NO. 40; GLYCERIN; PROPYLENE GLYCOL; WATER; SACCHARIN SODIUM; SODIUM BENZOATE; SORBITOL

Major Pharmaceuticals Children’s Dimaphen DM Drug Facts

Active ingredients (in each 10 mL)

Brompheniramine maleate, USP 2 mg

Dextromethorphan HBr, USP 10 mg

Phenylephrine HCl, USP 5 mg

Purposes

Antihistamine

Cough suppressant

Nasal decongestant

Uses

- temporarily relieves cough due to minor throat and bronchial irritation occurring with a cold, and nasal congestion due to the common cold, hay fever or other upper respiratory allergies
- temporarily relieves these symptoms due to hay fever (allergic rhinitis):
- runny nose
- sneezing
- itchy, watery eyes
- itching of the nose or throat
- temporarily restores freer breathing through the nose

Warnings

Do not use

- if you are now taking a prescription monoamine oxidase inhibitor (MAOI) (certain drugs for depression, psychiatric, or emotional conditions, or Parkinson’s disease), or for 2 weeks after stopping the MAOI drug. If you do not know if your prescription drug contains an MAOI, ask a doctor or pharmacist before taking this product.
- to make a child sleepy

Ask a doctor before use if you have

- heart disease
- high blood pressure
- thyroid disease
- diabetes
- trouble urinating due to an enlarged prostate gland
- glaucoma
- cough that occurs with too much phlegm (mucus)
- a breathing problem such as emphysema or chronic bronchitis
- cough that lasts or is chronic such as occurs with smoking, asthma or emphysema

Ask a doctor or pharmacist before use if you are

taking sedatives or tranquilizers

When using this product

- do not use more than directed
- may cause marked drowsiness
- avoid alcoholic beverages
- alcohol, sedatives, and tranquilizers may increase drowsiness
- be careful when driving a motor vehicle or operating machinery
- excitability may occur, especially in children

Stop use and ask a doctor if

- you get nervous, dizzy, or sleepless
- symptoms do not get better within 7 days or are accompanied by fever
- cough lasts for more than 7 days, comes back, or is accompanied by fever, rash, or persistent headache. A persistent cough may be a sign of a serious condition.

If pregnant or breast-feeding,

ask a health professional before use.

Keep out of reach of children.

In case of overdose, get medical help or contact a Poison Control Center right away (1-800-222-1222).

Directions

- do not take more than 6 doses in any 24-hour period
- measure only with dosage cup provided
- keep dosage cup with product
- mL = milliliter

age | dose
adults and children 12 years and over | 20 mL every 4 hours
children 6 to under 12 years | 10 mL every 4 hours
children under 6 years | do not use

Other information

- each 10 mL contains: sodium 4 mg
- store at 20°-25°C (68°-77°F)

Inactive ingredients

anhydrous citric acid, edetate disodium, FD&C blue no. 1, FD&C red no. 40, flavor, glycerin, propylene glycol, purified water, saccharin sodium, sodium benzoate, sorbitol solution

Questions or comments?

1-800-616-2471

Principal Display Panel

Children’s

Dimaphen™ DM

ANTIHISTAMINE, Brompheniramine Maleate

COUGH SUPPRESSANT, Dextromethorphan HBr

NASAL DECONGESTANT, Phenylephrine HCl

Relieves – Nasal Symptoms

Stuffy Nose – Runny Nose

Sneezing

Plus Other Symptoms

Itchy, Watery Eyes

Cough

GRAPE FLAVOR

Alcohol-Free

6 yrs. and older

COMPARE TO the active ingredients of DIMETAPP® COLD & COUGH

4 FL. OZ. (118 mL.)